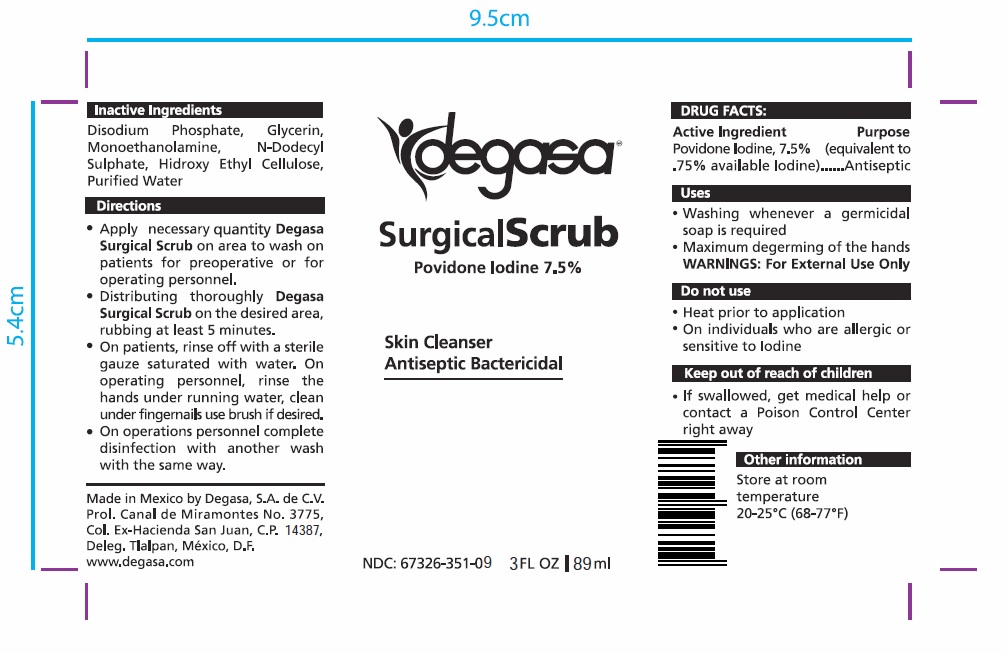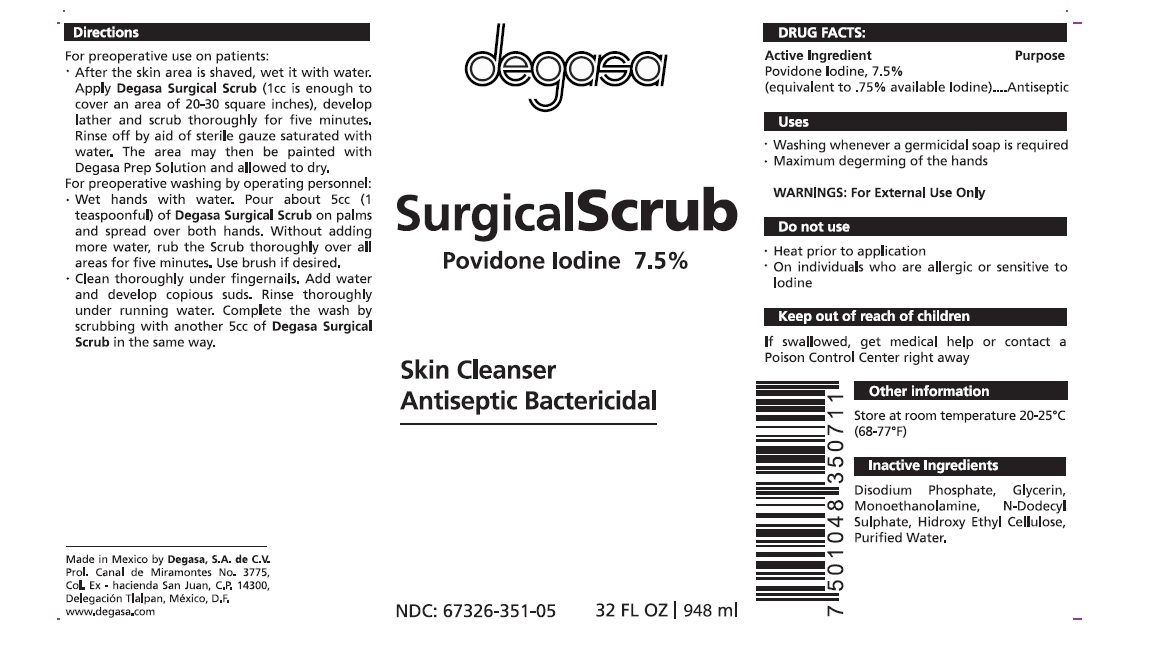 DRUG LABEL: 
                  Surgical Scrub
                
                  

NDC: 67326-351 | Form: SOLUTION
Manufacturer: Degasa SA De CV
Category: otc | Type: HUMAN OTC DRUG LABEL
Date: 20231105

ACTIVE INGREDIENTS: POVIDONE-IODINE 75 mg/1 mL
INACTIVE INGREDIENTS: SODIUM PHOSPHATE, DIBASIC, ANHYDROUS; GLYCERIN; MONOETHANOLAMINE; WATER

Surgical Scrub Skin Cleanser Antiseptic Bactericidal

Active Ingredient

Povidone Iodine, 7.5% (equivalent to .75% available Iodine)

Purpose

Antiseptic

Uses

- Washing whenever a germicidal soap is required
- Maximum degerming of the hands

WARNINGS:

For External Use Only

Keep out of reach of children

- If swallowed, get medical help or contact a Poison Control Center right away

Directions

- Apply necessary quantity on area to wash on patients for preoperative or for operating personnel. Degasa Surgical Scrub
- Distributing thoroughly on the desired area, rubbing at least 5 minutes. Degasa Surgical Scrub
- On patients, rinse off with a sterile gauze saturated with water. On operating personnel, rinse the hands under running water, clean under fingernails use brush if desired.
- On operations personnel complete disinfection with another wash with the same way.

Inactive ingredients

Disodium Phosphate, Glycerin, Monoethanolamine, N-Dodecyl Sulphate, Hidroxy Ethyl Cellulose, Purified Water